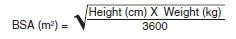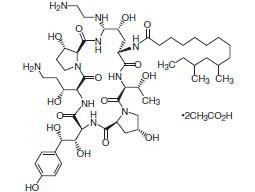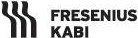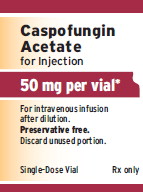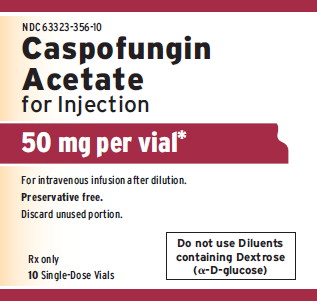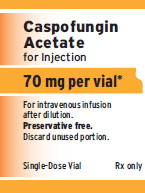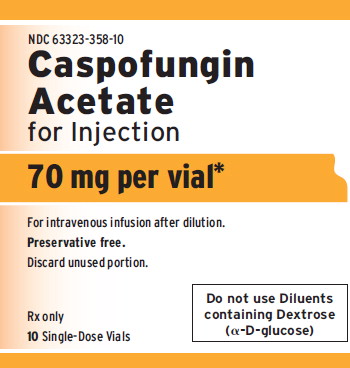 DRUG LABEL: Caspofungin Acetate
NDC: 63323-356 | Form: INJECTION, POWDER, LYOPHILIZED, FOR SOLUTION
Manufacturer: Fresenius Kabi USA, LLC
Category: prescription | Type: HUMAN PRESCRIPTION DRUG LABEL
Date: 20260108

ACTIVE INGREDIENTS: CASPOFUNGIN ACETATE 5 mg/1 mL
INACTIVE INGREDIENTS: ARGININE; HYDROCHLORIC ACID; SODIUM HYDROXIDE

HIGHLIGHTS OF PRESCRIBING INFORMATION

These highlights do not include all the information needed to use CASPOFUNGIN ACETATE FOR INJECTION safely and effectively. See full prescribing information for CASPOFUNGIN ACETATE FOR INJECTION.
CASPOFUNGIN ACETATE for injection, for intravenous use
Initial U.S. Approval: 2001

1 INDICATIONS AND USAGE

Caspofungin acetate for Injection is an echinocandin antifungal indicated in adults and pediatric patients (3 months of age and older) for:

- Empirical therapy for presumed fungal infections in febrile, neutropenic patients. (1)
- Treatment of candidemia and the following Candida infections: intra-abdominal abscesses, peritonitis and pleural space infections. (1)
- Treatment of esophageal candidiasis. (1)
- Treatment of invasive aspergillosis in patients who are refractory to or intolerant of other therapies. (1)

2 DOSAGE AND ADMINISTRATION

Important Administration Instructions for All Patients (2.1):

- Administer by slow intravenous (IV) infusion over approximately 1 hour. Do not administer by intravenous (IV) bolus administration.
- Do not mix or co-infuse Caspofungin acetate for Injection with other medications. Do not use diluents containing dextrose (α- D-glucose).

Dosage in Adults [18 years of age and older] (2.2):

- Administer a single 70 mg loading dose on Day 1, followed by 50 mg once daily for all indications except esophageal candidiasis.
- For esophageal candidiasis, use 50 mg once daily with no loading dose.

Dosage in Pediatric Patients [3 months to 17 years of age] (2.3):

- Dosing should be based on the patient's body surface area.
- For all indications, administer a single 70 mg/m2 loading dose on Day 1, followed by 50 mg/m2 once daily thereafter.
- Maximum loading dose and daily maintenance dose should not exceed 70 mg, regardless of the patient's calculated dose.

Dosage Adjustments in Patients with Hepatic Impairment (2.4):

Reduce dosage for adult patients with moderate hepatic impairment (35 mg once daily, with a 70 mg loading dose on Day 1 where appropriate).

Dosage Adjustments in Patients Receiving Concomitant Inducers of Hepatic CYP Enzymes (2.5):

- Use 70 mg once daily dose for adult patients on rifampin.
- Consider dose increase to 70 mg once daily for adult patients on nevirapine, efavirenz, carbamazepine, dexamethasone, or phenytoin.
- Pediatric patients receiving these same concomitant medications may also require an increase in dose to 70 mg/m2 once daily (maximum daily dose not to exceed 70 mg).

3 DOSAGE FORMS AND STRENGTHS

- For Injection: 50 or 70 mg lyophilized powder (plus allowance for overfill) in a single-dose vial for reconstitution. (3)

4 CONTRAINDICATIONS

- Caspofungin acetate for Injection is contraindicated in patients with known hypersensitivity to any component of this product. (4)

5 WARNINGS AND PRECAUTIONS

- Hypersensitivity: Anaphylaxis, possible histamine-mediated adverse reactions, including rash, facial swelling, angioedema, pruritus, sensation of warmth or bronchospasm, and cases of Stevens-Johnson syndrome (SJS) and toxic epidermal necrolysis (TEN) have been reported with use of caspofungin acetate for injection. Discontinue Caspofungin acetate for Injection at the first sign or symptom of a hypersensitivity reaction and administer appropriate treatment. (5.1)
- Hepatic Effects: Can cause abnormalities in liver enzymes. Isolated cases of hepatic dysfunction, hepatitis, or hepatic failure have been reported. Monitor patients who develop abnormal liver enzymes for evidence of worsening hepatic function and evaluate risk/benefit of continuing Caspofungin acetate for Injection. (5.2)
- Elevated Liver Enzymes during Concomitant use with Cyclosporine: Limit use to patients for whom potential benefit outweighs potential risk. Monitor patients who develop abnormal liver function tests (LFTs) during concomitant use with Caspofungin acetate for Injection. (5.3)

6 ADVERSE REACTIONS

- Adults: Most common adverse reactions (incidence 10% or greater) are diarrhea, pyrexia, ALT/AST increased, blood alkaline phosphatase increased, and blood potassium decreased. (6.1)
- Pediatric patients: Most common adverse reactions (incidence 10% or greater) are pyrexia, diarrhea, rash, ALT/AST increased, blood potassium decreased, hypotension, and chills. (6.1)

To report SUSPECTED ADVERSE REACTIONS, contact Fresenius Kabi USA, LLC at 1-800-551-7176 or FDA at 1-800-FDA-1088 or www.fda.gov/medwatch.

8 USE IN SPECIFIC POPULATIONS

- Pregnancy: Based on animal data, may cause fetal harm. (8.1)
- Pediatric Use: Safety and efficacy in neonates and infants less than 3 months old have not been established. (8.4)
- Hepatic Impairment: Reduce dose for adult patients with moderate hepatic impairment (35 mg once daily, with a 70 mg loading dose on Day 1 where appropriate). No data are available in adults with severe impairment or in pediatric patients with any degree of hepatic impairment. (2.4, 8.6,12.3)

FULL PRESCRIBING INFORMATION

1 INDICATIONS AND USAGE

1.1 Empirical Therapy for Presumed Fungal Infections in Febrile, Neutropenic Patients

Caspofungin acetate for Injection is indicated as empirical therapy for presumed fungal infections in febrile, neutropenic adult and pediatric patients (3 months of age and older) [see Clinical Studies (14.1,14.5)].

1.2 Treatment of Candidemia and Other Candida Infections

Caspofungin acetate for Injection is indicated for the treatment of candidemia and the following Candida infections: intra-abdominal abscesses, peritonitis, and pleural space infections in adult and pediatric patients (3 months of age and older) [see Clinical Studies (14.2, 14.5)].

Limitations of Use: Caspofungin acetate for Injection has not been studied in endocarditis, osteomyelitis, and meningitis due to Candida.

1.3 Treatment of Esophageal Candidiasis

Caspofungin acetate for Injection is indicated for the treatment of esophageal candidiasis in adult and pediatric patients (3 months of age and older) [see Clinical Studies (14.3, 14.5)].

Limitations of Use: Caspofungin acetate for Injection has not been approved for the treatment of oropharyngeal candidiasis (OPC). In the study that evaluated the efficacy of caspofungin in the treatment of esophageal candidiasis, patients with concomitant OPC had higher relapse rate of the OPC [see Clinical Studies (14.3)].

1.4 Treatment of Invasive Aspergillosis in Patients Who Are Refractory to or Intolerant of Other Therapies

Caspofungin acetate for Injection is indicated for the treatment of invasive aspergillosis in adult and pediatric patients (3 months of age and older) who are refractory to or intolerant of other therapies [see Clinical Studies (14.4,14.5)].

Limitations of Use: Caspofungin acetate for Injection has not been studied as initial therapy for invasive aspergillosis.

2 DOSAGE AND ADMINISTRATION

2.1 Important Administration Instructions for Use in All Patients

Administer Caspofungin acetate for Injection by slow intravenous (IV) infusion over approximately 1 hour. Do not administer Caspofungin acetate for Injection by intravenous (IV) bolus administration.

2.2 Recommended Dosage in Adult Patients [18 years of age and older]

The dosage and duration of Caspofungin acetate for Injection treatment for each indication are as follows:

Empirical Therapy for Presumed Fungal Infections in Febrile Neutropenic Patients

Administer a single 70 mg loading dose on Day 1, followed by 50 mg once daily thereafter. Duration of treatment should be based on the patient's clinical response. Continue empirical therapy until resolution of neutropenia. In general, treat patients found to have a fungal infection for a minimum of 14 days after the last positive culture and continue treatment for at least 7 days after both neutropenia and clinical symptoms are resolved. If the 50 mg dose is well tolerated but does not provide an adequate clinical response, the daily dose can be increased to 70 mg.

Candidemia and Other Candida Infections

Administer a single 70 mg loading dose on Day 1, followed by 50 mg once daily thereafter. Duration of treatment should be dictated by the patient's clinical and microbiological response. In general, continue antifungal therapy for at least 14 days after the last positive culture. Patients with neutropenia who remain persistently neutropenic may warrant a longer course of therapy pending resolution of the neutropenia.

Esophageal Candidiasis

The dose is 50 mg once daily for 7 to 14 days after symptom resolution. A 70 mg loading dose has not been studied for this indication. Because of the risk of relapse of oropharyngeal candidiasis in patients with HIV infections, suppressive oral therapy could be considered [see Clinical Studies (14.3)].

Invasive Aspergillosis

Administer a single 70 mg loading dose on Day 1, followed by 50 mg once daily thereafter. Duration of treatment should be based upon the severity of the patient's underlying disease, recovery from immunosuppression, and clinical response.

2.3 Recommended Dosing in Pediatric Patients [3 months to 17 years of age]

For all indications, administer a single 70 mg/m^2 loading dose on Day 1, followed by 50 mg/m^2 once daily thereafter. The maximum loading dose and the daily maintenance dose should not exceed 70 mg, regardless of the patient's calculated dose. Dosing in pediatric patients (3 months to 17 years of age) should be based on the patient's body surface area (BSA) as calculated by the Mosteller Formula [see References (15)]:

Following calculation of the patient's BSA, the loading dose in milligrams should be calculated as BSA (m^2) x 70 mg/m^2. The maintenance dose in milligrams should be calculated as BSA (m^2) x 50 mg/m^2.

Duration of treatment should be individualized to the indication, as described for each indication in adults [see Dosage and Administration (2.2)]. If the 50 mg/m^2 daily dose is well tolerated but does not provide an adequate clinical response, the daily dose can be increased to 70 mg/m^2 daily (not to exceed 70 mg).

2.4 Dosage Adjustments in Patients with Hepatic Impairment

Adult patients with mild hepatic impairment (Child-Pugh score 5 to 6) do not need a dosage adjustment. For adult patients with moderate hepatic impairment (Child-Pugh score 7 to 9), Caspofungin acetate for Injection 35 mg once daily is recommended based upon pharmacokinetic data [see Clinical Pharmacology (12.3)] with a 70 mg loading dose administered on Day 1 where appropriate. There is no clinical experience in adult patients with severe hepatic impairment (Child-Pugh score greater than 9) and in pediatric patients with any degree of hepatic impairment.

2.5 Dosage Adjustments in Patients Receiving Concomitant Inducers of Hepatic CYP Enzymes

Adult Patients:

Adult patients on rifampin should receive 70 mg of Caspofungin acetate for Injection once daily. When Caspofungin acetate for Injection is co-administered to adult patients with other inducers of hepatic CYP enzymes such as nevirapine, efavirenz, carbamazepine, dexamethasone, or phenytoin, administration of a daily dose of 70 mg of Caspofungin acetate for Injection should be considered [see Drug Interactions (7)].

Pediatric Patients:

Pediatric patients on rifampin should receive 70 mg/m^2 of Caspofungin acetate for Injection daily (not to exceed an actual daily dose of 70 mg). When Caspofungin acetate for Injection is co-administered to pediatric patients with other inducers of hepatic CYP enzymes, such as efavirenz, nevirapine, phenytoin, dexamethasone, or carbamazepine, a Caspofungin acetate for Injection dose of 70 mg/m^2 once daily (not to exceed 70 mg) should be considered [see Drug Interactions (7)].

2.6 Preparation for Administration

Reconstitution of Caspofungin Acetate for Injection for Intravenous Infusion

A. Aseptically add 10.8 mL of 0.9% Sodium Chloride Injection, Sterile Water for Injection, Bacteriostatic Water for Injection with methylparaben and propylparaben, or Bacteriostatic Water for Injection with 0.9% benzyl alcohol to the vial.
B. Each vial of Caspofungin acetate for Injection contains an intentional overfill of Caspofungin acetate for Injection. Thus, the drug concentration of the resulting solution is listed in Table 1 below.

Table 1: Information for Preparation of Caspofungin Acetate for Injection
Caspofungin Acetate for Injection vial (equivalent to caspofungin) | Volume of diluent to be added* | Resulting Concentration following Reconstitution
50 mg | 10.8 mL | 5 mg/mL
70 mg | 10.8 mL | 7 mg/mL
*Reconstitution volume of diluent to be added is based on the overfill amount of caspofungin (54.6 mg and 77.2 mg, respectively).

C. The white to off-white cake will dissolve completely. Mix gently until a clear solution is obtained. Visually inspect the reconstituted solution for particulate matter or discoloration during reconstitution and prior to infusion. Do not use if the solution is cloudy or has precipitated.
D. The reconstituted solution of Caspofungin acetate for Injection in the vial may be stored for up to one hour at ≤ 25°C (≤ 77°F) prior to the preparation of the infusion solution in the intravenous bag or bottle.
E. Caspofungin acetate for Injection vials are for single-dose only. Discard unused portion.

Dilution of the Reconstituted Solution in the Intravenous Bag for Infusion

A. Aseptically transfer the appropriate volume (mL) of reconstituted Caspofungin acetate for Injection to an intravenous (IV) bag (or bottle) containing 250 mL of 0.9%, 0.45%, or 0.225% Sodium Chloride Injection or Lactated Ringers Injection.
B. Alternatively, the volume (mL) of reconstituted Caspofungin acetate for Injection can be added to a reduced volume of 0.9%, 0.45%, or 0.225% Sodium Chloride Injection or Lactated Ringers Injection, not to exceed a final concentration of 0.5 mg/mL.
C. This diluted infusion solution in the intravenous bag or bottle must be used within 24 hours if stored at ≤ 25°C (≤ 77°F) or within 48 hours if stored refrigerated at 2° to 8°C (36° to 46°F).

Important Reconstitution and Dilution Instructions for Pediatric Patients 3 Months of Age and Older

Follow the reconstitution procedures described above using either the 70 mg or 50 mg vial to create the reconstituted solution [see Dosage and Administration (2.3)]. From the reconstituted solution in the vial, remove the volume of drug equal to the calculated loading dose or calculated maintenance dose based on a concentration of 7 mg/mL (if reconstituted from the 70 mg vial) or a concentration of 5 mg/mL (if reconstituted from the 50 mg vial).

The choice of vial should be based on total milligram dose of drug to be administered to the pediatric patient. To help ensure accurate dosing, it is recommended for pediatric doses less than 50 mg that 50 mg vials (with a concentration of 5 mg/mL) be used if available. The 70 mg vial should be reserved for pediatric patients requiring doses greater than 50 mg.

The maximum loading dose and the daily maintenance dose should not exceed 70 mg, regardless of the patient's calculated dose.

2.7 Drug Incompatibilities

Do not mix or co-infuse Caspofungin acetate for Injection with other medications, as there are no data available on the compatibility of Caspofungin acetate for Injection with other intravenous substances, additives, or medications.

Do not use diluents containing dextrose (α-D-glucose), as Caspofungin acetate for Injection is not stable in diluents containing dextrose.

3 DOSAGE FORMS AND STRENGTHS

Caspofungin acetate for Injection, 50 mg, is a white to off-white lyophilized cake or powder for reconstitution in a single-dose glass vial, which contains 50 mg of caspofungin equivalent to 55.5 mg of caspofungin acetate.

Caspofungin acetate for Injection, 70 mg, is a white to off-white lyophilized cake or powder for reconstitution in a single-dose glass vial, which contains 70 mg of caspofungin equivalent to 77.7 mg of caspofungin acetate.

4 CONTRAINDICATIONS

Caspofungin acetate for Injection is contraindicated in patients with known hypersensitivity (e.g., anaphylaxis) to any component of this product [see Adverse Reactions (6)].

5 WARNINGS AND PRECAUTIONS

5.1 Hypersensitivity

Anaphylaxis and other hypersensitivity reactions have been reported during administration of caspofungin acetate for injection. Possible histamine-mediated adverse reactions, including rash, facial swelling, angioedema, pruritus, sensation of warmth or bronchospasm have been reported.

Cases of Stevens-Johnson syndrome (SJS) and toxic epidermal necrolysis (TEN), some with a fatal outcome, have been reported with use of caspofungin acetate for injection [see Adverse Reactions (6.2)].

Discontinue Caspofungin acetate for Injection at the first sign or symptom of a hypersensitivity reaction and administer appropriate treatment.

5.2 Hepatic Effects

Laboratory abnormalities in liver function tests have been seen in healthy volunteers and in adult and pediatric patients treated with caspofungin acetate for injection. In some adult and pediatric patients with serious underlying conditions who were receiving multiple concomitant medications with caspofungin acetate for injection, isolated cases of clinically significant hepatic dysfunction, hepatitis, and hepatic failure have been reported; a causal relationship to caspofungin acetate for injection has not been established. Monitor patients who develop abnormal liver function tests during Caspofungin acetate for Injection therapy for evidence of worsening hepatic function and evaluated for risk/benefit of continuing Caspofungin acetate for Injection therapy.

5.3 Elevated Liver Enzymes During Concomitant Use with Cyclosporine

Elevated liver enzymes have occurred in patients receiving caspofungin acetate for injection and cyclosporine concomitantly. Only use Caspofungin acetate for Injection and cyclosporine in those patients for whom the potential benefit outweighs the potential risk. Patients who develop abnormal liver enzymes during concomitant therapy should be monitored and the risk/benefit of continuing therapy should be evaluated.

6 ADVERSE REACTIONS

The following serious adverse reactions are discussed in detail in another section of the labeling:

- Hypersensitivity [see Warnings and Precautions (5.1)]
- Hepatic Effects [see Warnings and Precautions (5.2)]
- Elevated Liver Enzymes During Concomitant Use with Cyclosporine [see Warnings and Precautions (5.3)]

6.1 Clinical Trials Experience

Because clinical trials are conducted under widely varying conditions, adverse reaction rates observed in clinical trials of caspofungin acetate for injection cannot be directly compared to rates in clinical trials of another drug and may not reflect the rates observed in practice.

Clinical Trials Experience in Adults

The overall safety of caspofungin acetate for injection was assessed in 1,865 adult individuals who received single or multiple doses of caspofungin acetate for injection: 564 febrile, neutropenic patients (empirical therapy study); 382 patients with candidemia and/or intra-abdominal abscesses, peritonitis, or pleural space infections (including 4 patients with chronic disseminated candidiasis); 297 patients with esophageal and/or oropharyngeal candidiasis; 228 patients with invasive aspergillosis; and 394 individuals in phase I studies. In the empirical therapy study patients had undergone hematopoietic stem-cell transplantation or chemotherapy. In the studies involving patients with documented Candida infections, the majority of the patients had serious underlying medical conditions (e.g., hematologic or other malignancy, recent major surgery, HIV) requiring multiple concomitant medications.

Patients in the noncomparative Aspergillus studies often had serious predisposing medical conditions (e.g., bone marrow or peripheral stem cell transplants, hematologic malignancy, solid tumors or organ transplants) requiring multiple concomitant medications.

Empirical Therapy for Presumed Fungal Infections in Febrile Neutropenic Patients

In the randomized, double-blinded empirical therapy study, patients received either caspofungin acetate for injection 50 mg/day (following a 70 mg loading dose) or AmBisome® (amphotericin B liposome for injection, 3 mg/kg/day). In this study clinical or laboratory hepatic adverse reactions were reported in 39% and 45% of patients in the caspofungin acetate for injection and AmBisome groups, respectively. Also reported was an isolated, serious adverse reaction of hyperbilirubinemia. Adverse reactions occurring in 7.5% or greater of the patients in either treatment group are presented in Table 2.

Table 2: Adverse Reactions Among Patients with Persistent Fever and Neutropenia Incidence 7.5% or Greater for at Least One Treatment Group
Adverse Reactions | Caspofungin Acetate for Injection* N=564 (percent) | AmBisome† N=547 (percent)
All Systems, Any Adverse Reaction | 95 | 97
Investigations | 58 | 63
Alanine Aminotransferase Increased | 18 | 20
Blood Alkaline Phosphatase Increased | 15 | 23
Blood Potassium Decreased | 15 | 23
Aspartate Aminotransferase Increased | 14 | 17
Blood Bilirubin Increased | 10 | 14
Blood Magnesium Decreased | 7 | 9
Blood Glucose Increased | 6 | 9
Bilirubin Conjugated Increased | 5 | 9
Blood Urea Increased | 4 | 8
Blood Creatinine Increased | 3 | 11
General Disorders and Administration Site Conditions | 57 | 63
Pyrexia | 27 | 29
Chills | 23 | 31
Edema Peripheral | 11 | 12
Mucosal Inflammation | 6 | 8
Gastrointestinal Disorders | 50 | 55
Diarrhea | 20 | 16
Nausea | 11 | 20
Abdominal Pain | 9 | 11
Vomiting | 9 | 17
Respiratory, Thoracic and Mediastinal Disorders | 47 | 49
Dyspnea | 9 | 10
Skin and Subcutaneous Tissue Disorders | 42 | 37
Rash | 16 | 14
Nervous System Disorders | 25 | 27
Headache | 11 | 12
Metabolism and Nutrition Disorders | 21 | 24
Hypokalemia | 6 | 8
Vascular Disorders | 20 | 23
Hypotension | 6 | 10
Cardiac Disorders | 16 | 19
Tachycardia | 7 | 9
Within any system organ class, individuals may experience more than 1 adverse reaction.
* 70 mg on Day 1, then 50 mg once daily for the remainder of treatment; daily dose was increased to 70 mg for 73 patients.
†3 mg/kg/day; daily dose was increased to 5 mg/kg for 74 patients.

The proportion of patients who experienced an infusion-related adverse reaction (defined as a systemic event, such as pyrexia, chills, flushing, hypotension, hypertension, tachycardia, dyspnea, tachypnea, rash, or anaphylaxis, that developed during the study therapy infusion and one hour following infusion) was significantly lower in the group treated with caspofungin acetate for injection (35%) than in the group treated with AmBisome (52%).

To evaluate the effect of caspofungin acetate for injection and AmBisome on renal function, nephrotoxicity was defined as doubling of serum creatinine relative to baseline or an increase of greater than or equal to 1 mg/dL in serum creatinine if baseline serum creatinine was above the upper limit of the normal range. Among patients whose baseline creatinine clearance was greater than 30 mL/min, the incidence of nephrotoxicity was significantly lower in the group treated with caspofungin acetate for injection (3%) than in the group treated with AmBisome (12%).

Candidemia and Other Candida Infections

In the randomized, double-blinded invasive candidiasis study, patients received either caspofungin acetate for injection 50 mg/day (following a 70 mg loading dose) or amphotericin B 0.6 to 1 mg/kg/day. Adverse reactions occurring in 10% or greater of the patients in either treatment group are presented in Table 3.

Table 3: Adverse Reactions Among Patients with Candidemia or other Candida Infections* Incidence 10% or Greater for at Least One Treatment Group
Adverse Reactions | Caspofungin Acetate for Injection 50 mg† N=114 (percent) | Amphotericin B N=125 (percent)
All Systems, Any Adverse Reaction | 96 | 99
Investigations | 67 | 82
Blood Potassium Decreased | 23 | 32
Blood Alkaline Phosphatase Increased | 21 | 32
Hemoglobin Decreased | 18 | 23
Alanine Aminotransferase Increased | 16 | 15
Aspartate Aminotransferase Increased | 16 | 14
Blood Bilirubin Increased | 13 | 17
Hematocrit Decreased | 13 | 18
Blood Creatinine Increased | 11 | 28
Red Blood Cells Urine Positive | 10 | 10
Blood Urea Increased | 9 | 23
Bilirubin Conjugated Increased | 8 | 14
Gastrointestinal Disorders | 49 | 53
Vomiting | 17 | 16
Diarrhea | 14 | 10
Nausea | 9 | 17
General Disorders and Administration Site Conditions | 47 | 63
Pyrexia | 13 | 33
Edema Peripheral | 11 | 12
Chills | 9 | 30
Respiratory, Thoracic and Mediastinal Disorders | 40 | 54
Tachypnea | 1 | 11
Cardiac Disorders | 26 | 34
Tachycardia | 8 | 12
Skin and Subcutaneous Tissue Disorders | 25 | 28
Rash | 4 | 10
Vascular Disorders | 25 | 38
Hypotension | 10 | 16
Blood and Lymphatic System Disorders | 15 | 13
Anemia | 11 | 9
Within any system organ class, individuals may experience more than 1 adverse reaction.
* Intra-abdominal abscesses, peritonitis and pleural space infections.
† Patients received caspofungin acetate for injection 70 mg on Day 1, then 50 mg once daily for the remainder of their treatment.

The proportion of patients who experienced an infusion-related adverse reaction (defined as a systemic event, such as pyrexia, chills, flushing, hypotension, hypertension, tachycardia, dyspnea, tachypnea, rash, or anaphylaxis, that developed during the study therapy infusion and one hour following infusion) was significantly lower in the group treated with caspofungin acetate for injection (20%) than in the group treated with amphotericin B (49%).

To evaluate the effect of caspofungin acetate for injection and amphotericin B on renal function, nephrotoxicity was defined as doubling of serum creatinine relative to baseline or an increase of greater than or equal to 1 mg/dL in serum creatinine if baseline serum creatinine was above the upper limit of the normal range. In a subgroup of patients whose baseline creatinine clearance was greater than 30 mL/min, the incidence of nephrotoxicity was significantly lower in the group treated with caspofungin acetate for injection than in the group treated with amphotericin B.

In a second randomized, double-blinded invasive candidiasis study, patients received either caspofungin acetate for injection 50 mg/day (following a 70 mg loading dose) or caspofungin acetate for injection 150 mg/day. The proportion of patients who experienced any adverse reaction was similar in the 2 treatment groups; however, this study was not large enough to detect differences in rare or unexpected adverse reactions. Adverse reactions occurring in 5% or greater of the patients in either treatment group are presented in Table 4.

Table 4: Adverse Reactions Among Patients with Candidemia or other Candida Infections* Incidence 5% or Greater for at Least One Treatment Group
Adverse Reactions | Caspofungin Acetate for Injection 50 mg†N=104 (percent) | Caspofungin Acetate for Injection 150 mg N=100 (percent)
All Systems, Any Adverse Reaction | 83 | 83
General Disorders and Administration Site Conditions | 33 | 27
Pyrexia | 6 | 6
Gastrointestinal Disorders | 30 | 33
Vomiting | 11 | 6
Diarrhea | 6 | 7
Nausea | 5 | 7
Investigations | 28 | 35
Alkaline Phosphatase Increased | 12 | 9
Aspartate Aminotransferase Increased | 6 | 9
Blood Potassium Decreased | 6 | 8
Alanine Aminotransferase Increased | 4 | 7
Vascular Disorders | 19 | 18
Hypotension | 7 | 3
Hypertension | 5 | 6
Within any system organ class, individuals may experience more than 1 adverse event.
* Intra-abdominal abscesses, peritonitis and pleural space infections.
† Patients received caspofungin acetate for injection 70 mg on Day 1, then 50 mg once daily for the remainder of their treatment.

Esophageal Candidiasis and Oropharyngeal Candidiasis

Adverse reactions occurring in 10% or greater of patients with esophageal and/or oropharyngeal candidiasis are presented in Table 5.

Table 5: Adverse Reactions Among Patients with Esophageal and/or Oropharyngeal Candidiasis Incidence 10% or Greater for at Least One Treatment Group
Adverse Reactions | Caspofungin Acetate for Injection 50 mg* N=83 (percent) | Fluconazole intravenous (IV) 200 mg* N=94 (percent)
All Systems, Any Adverse Reaction | 90 | 93
Gastrointestinal Disorders | 58 | 50
Diarrhea | 27 | 18
Nausea | 15 | 15
Investigations | 53 | 61
Hemoglobin Decreased | 21 | 16
Hematocrit Decreased | 18 | 16
Aspartate Aminotransferase Increased | 13 | 19
Blood Alkaline Phosphatase Increased | 13 | 17
Alanine Aminotransferase Increased | 12 | 17
White Blood Cell Count Decreased | 12 | 19
General Disorders and Administration Site Conditions | 31 | 36
Pyrexia | 21 | 21
Vascular Disorders | 19 | 15
Phlebitis | 18 | 11
Nervous System Disorders | 18 | 17
Headache | 15 | 9
Within any system organ class, individuals may experience more than 1 adverse reaction.
*Derived from a comparator-controlled clinical study.

Invasive Aspergillosis

In an open-label, noncomparative aspergillosis study, in which 69 patients received caspofungin acetate for injection (70 mg loading dose on Day 1 followed by 50 mg daily), the following adverse reactions were observed with an incidence of 12.5% or greater: blood alkaline phosphatase increased (22%), hypotension (20%), respiratory failure (20%), pyrexia (17%), diarrhea (15%), nausea (15%), headache (15%), rash (13%), alanine aminotransferase increased (13%), aspartate aminotransferase increased (13%), blood bilirubin increased (13%), and blood potassium decreased (13%). Also reported in this patient population were pulmonary edema, ARDS (adult respiratory distress syndrome), and radiographic infiltrates.

Clinical Trials Experience in Pediatric Patients (3 months to 17 years of age)

The overall safety of caspofungin acetate for injection was assessed in 171 pediatric patients who received single or multiple doses of caspofungin acetate for injection. The distribution among the 153 pediatric patients who were over the age of 3 months was as follows: 104 febrile, neutropenic patients; 38 patients with candidemia and/or intra-abdominal abscesses, peritonitis, or pleural space infections; 1 patient with esophageal candidiasis; and 10 patients with invasive aspergillosis. The overall safety profile of caspofungin acetate for injection in pediatric patients is comparable to that in adult patients. Table 6 shows the incidence of adverse reactions reported in 7.5% or greater of pediatric patients in clinical studies.

One patient (0.6%) receiving caspofungin acetate for injection, and three patients (12%) receiving AmBisome developed a serious drug-related adverse reaction. Two patients (1%) were discontinued from caspofungin acetate for injection and three patients (12%) were discontinued from AmBisome due to a drug-related adverse reaction. The proportion of patients who experienced an infusion-related adverse reaction (defined as a systemic event, such as pyrexia, chills, flushing, hypotension, hypertension, tachycardia, dyspnea, tachypnea, rash, or anaphylaxis, that developed during the study therapy infusion and one hour following infusion) was 22% in the group treated with caspofungin acetate for injection and 35% in the group treated with AmBisome.

Table 6: Adverse Reactions Among Pediatric Patients (0 months to 17 years of age) Incidence 7.5% or Greater for at Least One Treatment Group
Adverse Reactions | Noncomparative Clinical Studies | Comparator-Controlled Clinical Study of Empirical Therapy
Adverse Reactions | Caspofungin Acetate for Injection Any Dose N=115 (percent) | Caspofungin Acetate for Injection 50 mg/m2* N=56 (percent) | AmBisome 3 mg/kg N=26 (percent)
All Systems, Any Adverse Reaction | 95 | 96 | 89
Investigations | 55 | 41 | 50
Blood Potassium Decreased | 18 | 9 | 27
Aspartate Aminotransferase Increased | 17 | 2 | 12
Alanine Aminotransferase Increased | 14 | 5 | 12
Blood Potassium Increased | 3 | 0 | 8
General Disorders and Administration Site Conditions | 47 | 59 | 42
Pyrexia | 29 | 30 | 23
Chills | 10 | 13 | 8
Mucosal Inflammation | 10 | 4 | 4
Edema | 3 | 4 | 8
Gastrointestinal Disorders | 42 | 41 | 35
Diarrhea | 17 | 7 | 15
Vomiting | 8 | 11 | 12
Abdominal Pain | 7 | 4 | 12
Nausea | 4 | 4 | 8
Infections and Infestations | 40 | 30 | 35
Central Line Infection | 1 | 9 | 0
Skin and Subcutaneous Tissue Disorders | 33 | 41 | 39
Pruritus | 7 | 6 | 8
Rash | 6 | 23 | 8
Erythema | 4 | 9 | 0
Vascular Disorders | 24 | 21 | 19
Hypotension | 12 | 9 | 8
Hypertension | 10 | 9 | 4
Metabolism and Nutrition Disorders | 22 | 11 | 23
Hypokalemia | 8 | 5 | 4
Cardiac Disorders | 17 | 13 | 19
Tachycardia | 4 | 11 | 19
Nervous System Disorders | 13 | 16 | 8
Headache | 5 | 9 | 4
Musculoskeletal and Connective Tissue Disorders | 11 | 14 | 12
Back Pain | 4 | 0 | 8
Blood and Lymphatic System Disorders | 10 | 2 | 15
Anemia | 2 | 0 | 8
Within any system organ class, individuals may experience more than 1 adverse reaction.
* 70 mg/m^2 on Day 1, then 50 mg/m^2 once daily for the remainder of the treatment.

Overall Safety Experience of Caspofungin Acetate for Injection in Clinical Trials

The overall safety of caspofungin acetate for injection was assessed in 2,036 individuals (including 1,642 adult or pediatric patients and 394 volunteers) from 34 clinical studies. These individuals received single or multiple (once daily) doses of caspofungin acetate for injection, ranging from 5 mg to 210 mg. Full safety data is available from 1,951 individuals, as the safety data from 85 patients enrolled in 2 compassionate use studies was limited solely to serious adverse reactions.

Adverse reactions which occurred in 5% or greater of all individuals who received caspofungin acetate for injection in these trials are shown in Table 7.

Overall, 1,665 of the 1,951 (85%) patients/volunteers who received caspofungin acetate for injection experienced an adverse reaction.

Table 7: Adverse Reactions* in Patients Who Received Caspofungin Acetate for Injection in Clinical Trials†Incidence 5% or Greater for at Least One Treatment Group
Adverse Reactions‡ | Caspofungin Acetate for Injection (N = 1,951)
Adverse Reactions‡ | N | (%)
All Systems, Any Adverse Reaction | 1,665 | (85)
Investigations | 901 | (46)
Alanine Aminotransferase Increased | 258 | (13)
Aspartate Aminotransferase Increased | 233 | (12)
Blood Alkaline Phosphatase Increased | 232 | (12)
Blood Potassium Decreased | 220 | (11)
Blood Bilirubin Increased | 117 | (6)
General Disorders and Administration Site Conditions | 843 | (43)
Pyrexia | 381 | (20)
Chills | 192 | (10)
Edema Peripheral | 110 | (6)
Gastrointestinal Disorders | 754 | (39)
Diarrhea | 273 | (14)
Nausea | 166 | (9)
Vomiting | 146 | (8)
Abdominal Pain | 112 | (6)
Infections and Infestations | 730 | (37)
Pneumonia | 115 | (6)
Respiratory, Thoracic, and Mediastinal Disorders | 613 | (31)
Cough | 111 | (6)
Skin and Subcutaneous Tissue Disorders | 520 | (27)
Rash | 159 | (8)
Erythema | 98 | (5)
Nervous System Disorders | 412 | (21)
Headache | 193 | (10)
Vascular Disorders | 344 | (18)
Hypotension | 118 | (6)
* Defined as an adverse reaction, regardless of causality, while on caspofungin acetate for injection or during the 14-day post-caspofungin follow-up period.
† Incidence for each preferred term is 5% or greater among individuals who received at least 1 dose of caspofungin acetate for injection.
‡ Within any system organ class, individuals may experience more than 1 adverse event.

Clinically significant adverse reactions, regardless of causality or incidence which occurred in less than 5% of patients are listed below.

- Blood and lymphatic system disorders: anemia, coagulopathy, febrile neutropenia, neutropenia, thrombocytopenia
- Cardiac disorders: arrhythmia, atrial fibrillation, bradycardia, cardiac arrest, myocardial infarction, tachycardia
- Gastrointestinal disorders: abdominal distension, abdominal pain upper, constipation, dyspepsia
- General disorders and administration site conditions: asthenia, fatigue, infusion site pain/pruritus/swelling, mucosal inflammation, edema
- Hepatobiliary disorders: hepatic failure, hepatomegaly, hepatotoxicity, hyperbilirubinemia, jaundice
- Infections and infestations: bacteremia, sepsis, urinary tract infection
- Metabolic and nutrition disorders: anorexia, decreased appetite, fluid overload, hypomagnesemia, hypercalcemia, hyperglycemia, hypokalemia
- Musculoskeletal, connective tissue, and bone disorders: arthralgia, back pain, pain in extremity
- Nervous system disorders: convulsion, dizziness, somnolence, tremor
- Psychiatric disorders: anxiety, confusional state, depression, insomnia
- Renal and urinary disorders: hematuria, renal failure
- Respiratory, thoracic, and mediastinal disorders: dyspnea, epistaxis, hypoxia, tachypnea
- Skin and subcutaneous tissue disorders: erythema, petechiae, skin lesion, urticaria
- Vascular disorders: flushing, hypertension, phlebitis

6.2 Postmarketing Experience

The following additional adverse reactions have been identified during the post-approval use of caspofungin acetate for injection. Because these reactions are reported voluntarily from a population of uncertain size, it is not always possible to reliably estimate their frequency or establish a causal relationship to drug exposure.

- Gastrointestinal disorders: pancreatitis
- Hepatobiliary disorders: hepatic necrosis
- Skin and subcutaneous tissue disorders: erythema multiforme, toxic epidermal necrolysis, Stevens- Johnson syndrome, and skin exfoliation
- Renal and urinary disorders: clinically significant renal dysfunction
- General disorders and administration site conditions: swelling and peripheral edema
- Laboratory abnormalities: gamma-glutamyltransferase increased

7 DRUG INTERACTIONS

Cyclosporine: In two adult clinical studies, cyclosporine (one 4 mg/kg dose or two 3 mg/kg doses) increased the AUC of caspofungin acetate for injection. Caspofungin acetate for injection did not increase the plasma levels of cyclosporine. There were transient increases in liver ALT and AST when caspofungin acetate for injection and cyclosporine were co-administered. Monitor patients who develop abnormal liver enzymes during concomitant therapy and evaluate the risk/benefit of continuing therapy [see Warnings and Precautions (5.2) and Clinical Pharmacology (12.3)].

Tacrolimus: For patients receiving Caspofungin acetate for Injection and tacrolimus, standard monitoring of tacrolimus trough whole blood concentrations and appropriate tacrolimus dosage adjustments are recommended.

Inducers of Hepatic CYP Enzymes

Rifampin: Rifampin is a potent CYP3A4 inducer and concomitant administration with caspofungin acetate for injection is expected to reduce the plasma concentrations of caspofungin acetate for injection. Therefore, adult patients on rifampin should receive 70 mg of Caspofungin acetate for Injection daily and pediatric patients on rifampin should receive 70 mg/m^2 of Caspofungin acetate for Injection daily (not to exceed an actual daily dose of 70 mg) [see Dosage and Administration (2.5) and Clinical Pharmacology (12.3)].

Other Inducers of Hepatic CYP Enzymes

Adults: When Caspofungin acetate for Injection is co-administered to adult patients with other inducers of hepatic CYP enzymes, such as efavirenz, nevirapine, phenytoin, dexamethasone, or carbamazepine, administration of a daily dose of 70 mg of Caspofungin acetate for Injection should be considered [see Dosage and Administration (2.5) and Clinical Pharmacology (12.3)].

Pediatric Patients: When Caspofungin acetate for Injection is co-administered to pediatric patients with other inducers of hepatic CYP enzymes, such as efavirenz, nevirapine, phenytoin, dexamethasone, or carbamazepine, administration of a daily dose of 70 mg/m^2 Caspofungin acetate for Injection (not to exceed an actual daily dose of 70 mg) should be considered [see Dosage and Administration (2.5) and Clinical Pharmacology (12.3)].

8 USE IN SPECIFIC POPULATIONS

8.1 Pregnancy

Risk Summary

Based on animal data, Caspofungin acetate for Injection may cause fetal harm (see Data). There are insufficient human data to establish whether there is a drug-associated risk for major birth defects, miscarriage, or adverse maternal or fetal outcomes with Caspofungin acetate for Injection use in pregnant women.

In animal studies, caspofungin caused embryofetal toxicity, including increased resorptions, increased peri- implantation loss, and incomplete ossification at multiple fetal sites when administered intravenously to pregnant rats and rabbits during organogenesis at doses up to 0.8 and 2 times the clinical dose, respectively (see Data). Advise patients of the potential risk to the fetus.

The estimated background risk of major birth defects and miscarriage for the indicated population is unknown. All pregnancies have a background risk of birth defect, loss, or other adverse outcomes. In the U.S. general population, the estimated background risk of major birth defects and miscarriage in clinically recognized pregnancies is 2 to 4% and 15 to 20%, respectively.

Data

Animal Data

In animal reproduction studies, pregnant rats dosed intravenously with caspofungin during organogenesis (gestational days [GD] 6 to 20) at 0.5, 2, or 5 mg/kg/day (up to 0.8 times the clinical dose based on body surface area comparison) showed increased resorptions and peri-implantation losses at 5 mg/kg/day. Incomplete ossification of the skull and torso and increased incidences of cervical rib were noted in offspring born to pregnant rats treated at doses up to 5 mg/kg/day. In pregnant rabbits treated with intravenous caspofungin during organogenesis (GD 7 to 20) at doses of 1, 3, or 6 mg/kg/day (approximately 2 times the clinical dose based on body surface area comparison), increased fetal resorptions and increased incidence of incomplete ossification of the talus/calcaneus in offspring were observed at the highest dose tested. Caspofungin crossed the placenta in rats and rabbits and was detectable in fetal plasma.

In peri- and postnatal development study in rats, intravenous caspofungin administered at 0.5, 2 or 5 mg/kg/day from Day 6 of gestation through Day 20 of lactation was not associated with any adverse effects on reproductive performance or subsequent development of first generation (F1) offspring or malformations in second generation (F2) offspring.

8.2 Lactation

Risk Summary

There are no data on the presence of caspofungin in human milk, the effects on the breast-fed child, or the effects on milk production. Caspofungin was found in the milk of lactating, drug-treated rats.

The developmental and health benefits of breastfeeding should be considered along with the mother's clinical need for Caspofungin acetate for Injection and any potential adverse effects on the breastfed child from Caspofungin acetate for Injection or from the underlying maternal condition.

8.4 Pediatric Use

The safety and effectiveness of caspofungin acetate for injection in pediatric patients 3 months to 17 years of age are supported by evidence from adequate and well-controlled studies in adults, pharmacokinetic data in pediatric patients, and additional data from prospective studies in pediatric patients 3 months to 17 years of age for the following indications [see Indications and Usage (1)]:

- Empirical therapy for presumed fungal infections in febrile, neutropenic patients.
- Treatment of candidemia and the following Candida infections: intra-abdominal abscesses, peritonitis, and pleural space infections.
- Treatment of esophageal candidiasis.
- Treatment of invasive aspergillosis in patients who are refractory to or intolerant of other therapies (e.g., amphotericin B, lipid formulations of amphotericin B, itraconazole).

The efficacy and safety of caspofungin acetate for injection has not been adequately studied in prospective clinical trials involving neonates and infants under 3 months of age. Although limited pharmacokinetic data were collected in neonates and infants below 3 months of age, these data are insufficient to establish a safe and effective dose of caspofungin in the treatment of neonatal candidiasis. Invasive candidiasis in neonates has a higher rate of CNS and multi-organ involvement than in older patients; the ability of caspofungin acetate for injection to penetrate the blood-brain barrier and to treat patients with meningitis and endocarditis is unknown.

Caspofungin acetate for injection has not been studied in pediatric patients with endocarditis, osteomyelitis, and meningitis due to Candida. Caspofungin acetate for injection has also not been studied as initial therapy for invasive aspergillosis in pediatric patients.

In clinical trials, 171 pediatric patients (0 months to 17 years of age), including 18 patients who were less than 3 months of age, were given intravenous caspofungin acetate for injection. Pharmacokinetic studies enrolled a total of 66 pediatric patients, and an additional 105 pediatric patients received caspofungin acetate for injection in safety and efficacy studies [see Clinical Pharmacology (12.3) and Clinical Studies (14.5)]. The majority of the pediatric patients received caspofungin acetate for injection at a once-daily maintenance dose of 50 mg/m^2 for a mean duration of 12 days (median 9, range 1 to 87 days). In all studies, safety was assessed by the investigator throughout study therapy and for 14 days following cessation of study therapy. The most common adverse reactions in pediatric patients treated with caspofungin acetate for injection were pyrexia (29%), blood potassium decreased (15%), diarrhea (14%), increased aspartate aminotransferase (12%), rash (12%), increased alanine aminotransferase (11%), hypotension (11%), and chills (11%) [see Adverse Reactions (6.2)].

Postmarketing hepatobiliary adverse reactions have been reported in pediatric patients with serious underlying medical conditions [see Warnings and Precautions (5.3)].

8.5 Geriatric Use

Clinical studies of caspofungin acetate for injection did not include sufficient numbers of patients aged 65 and over to determine whether they respond differently from younger patients. Although the number of elderly patients was not large enough for a statistical analysis, no overall differences in safety or efficacy were observed between these and younger patients. Plasma concentrations of caspofungin in healthy older men and women (65 years of age and older) were increased slightly (approximately 28% in AUC) compared to young healthy men. A similar effect of age on pharmacokinetics was seen in patients with candidemia or other Candida infections (intra-abdominal abscesses, peritonitis, or pleural space infections). No dose adjustment is recommended for the elderly; however, greater sensitivity of some older individuals cannot be ruled out.

8.6 Patients with Hepatic Impairment

Adult patients with mild hepatic impairment (Child-Pugh score 5 to 6) do not need a dosage adjustment. For adult patients with moderate hepatic impairment (Child-Pugh score 7 to 9), Caspofungin acetate for Injection 35 mg once daily is recommended based upon pharmacokinetic data [see Clinical Pharmacology (12.3)].

However, where recommended, a 70 mg loading dose should still be administered on Day 1 [see Dosage and Administration (2.4) and Clinical Pharmacology (12.3)]. There is no clinical experience in adult patients with severe hepatic impairment (Child-Pugh score greater than 9) and in pediatric patients 3 months to 17 years of age with any degree of hepatic impairment.

8.7 Patients with Renal Impairment

No dosage adjustment is necessary for patients with renal impairment. Caspofungin is not dialyzable; thus, supplementary dosing is not required following hemodialysis [see Clinical Pharmacology (12.3)].

10 OVERDOSAGE

In 6 healthy subjects who received a single 210 mg dose, no significant adverse reactions were reported Multiple doses above 150 mg daily have not been studied. Caspofungin is not dialyzable.

In clinical trials, one pediatric patient (16 years of age) unintentionally received a single dose of caspofungin of 113 mg (on Day 1), followed by 80 mg daily for an additional 7 days. No clinically significant adverse reactions were reported.

11 DESCRIPTION

Caspofungin acetate for Injection is a sterile, lyophilized product for intravenous (IV) infusion that contains a semisynthetic lipopeptide (echinocandin) compound synthesized from a fermentation product of Glarea lozoyensis. Caspofungin acetate for Injection is an echinocandin antifungal that inhibits the synthesis of β (1,3)- D-glucan, an integral component of the fungal cell wall.

Caspofungin acetate is 1-[(4R,5S)-5-[(2-aminoethyl)amino]-N^2-(10,12-dimethyl-1-oxotetradecyl)-4-hydroxy- L-ornithine]-5-[(3R)-3-hydroxy-L-ornithine] pneumocandin B0 diacetate (salt). Each vial of Caspofungin acetate for Injection, 50 mg, contains 50 mg of caspofungin equivalent to 55.5 mg of caspofungin acetate, arginine (100 mg), and hydrochloric acid/sodium hydroxide required for pH adjustment. Each vial of Caspofungin acetate for injection, 70 mg, contains 70 mg of caspofungin equivalent to 77.7 mg of caspofungin acetate, arginine (140 mg), and hydrochloric acid/sodium hydroxide required for pH adjustment. Caspofungin acetate is a hygroscopic, white to off-white powder. It is freely soluble in water and methanol, and slightly soluble in ethanol. The pH of a saturated aqueous solution of caspofungin acetate is approximately 6.6. The structural formula is:

C52H88N10O15•2C2H4O2 M.W. 1213.42

12 CLINICAL PHARMACOLOGY

12.1 Mechanism of Action

Caspofungin is an echinocandin antifungal drug [see Microbiology (12.4)].

12.3 Pharmacokinetics

Adult and pediatric pharmacokinetic parameters are presented in Table 8.

Distribution

Plasma concentrations of caspofungin decline in a polyphasic manner following single 1 hour intravenous infusions. A short α-phase occurs immediately postinfusion, followed by a β-phase (half-life of 9 to 11 hours) that characterizes much of the profile and exhibits clear log-linear behavior from 6 to 48 hours postdose during which the plasma concentration decreases 10-fold. An additional, longer half-life phase, y-phase, (half-life of 40 to 50 hours), also occurs. Distribution, rather than excretion or biotransformation, is the dominant mechanism influencing plasma clearance. Caspofungin is extensively bound to albumin (approximately 97%), and distribution into red blood cells is minimal. Mass balance results showed that approximately 92% of the administered radioactivity was distributed to tissues by 36 to 48 hours after a single 70 mg dose of [^3H] caspofungin acetate for injection. There is little excretion or biotransformation of caspofungin during the first 30 hours after administration.

Metabolism

Caspofungin is slowly metabolized by hydrolysis and N-acetylation. Caspofungin also undergoes spontaneous chemical degradation to an open-ring peptide compound, L-747969. At later time points (5 or more days postdose), there is a low level (7 or less picomoles/mg protein, or 1.3% or less of the administered dose) of covalent binding of radiolabel in plasma following single-dose administration of [^3H] caspofungin acetate for injection, which may be due to two reactive intermediates formed during the chemical degradation of caspofungin to L- 747969. Additional metabolism involves hydrolysis into constitutive amino acids and their degradates, including dihydroxyhomotyrosine and N-acetyl-dihydroxyhomotyrosine. These two tyrosine derivatives are found only in urine, suggesting rapid clearance of these derivatives by the kidneys.

Excretion

Two single-dose radiolabeled pharmacokinetic studies were conducted. In one study, plasma, urine, and feces were collected over 27 days, and in the second study plasma was collected over 6 months. Plasma concentrations of radioactivity and of caspofungin were similar during the first 24 to 48 hours postdose; thereafter drug levels fell more rapidly. In plasma, caspofungin concentrations fell below the limit of quantitation after 6 to 8 days postdose, while radiolabel fell below the limit of quantitation at 22.3 weeks postdose. After single intravenous administration of [^3H] caspofungin acetate for injection, excretion of caspofungin and its metabolites in humans was 35% of dose in feces and 41% of dose in urine. A small amount of caspofungin is excreted unchanged in urine (approximately 1.4% of dose). Renal clearance of parent drug is low (approximately 0.15 mL/min) and total clearance of caspofungin is 12 mL/min.

Special Populations

Renal Impairment

In a clinical study of single 70 mg doses, caspofungin pharmacokinetics were similar in healthy adult volunteers with mild renal impairment (creatinine clearance 50 to 80 mL/min) and control subjects. Moderate (creatinine clearance 31 to 49 mL/min), severe (creatinine clearance 5 to 30 mL/min), and end-stage (creatinine clearance less than 10 mL/min and dialysis dependent) renal impairment moderately increased caspofungin plasma concentrations after single-dose administration (range: 30 to 49% for AUC). However, in adult patients with invasive aspergillosis, candidemia, or other Candida infections (intra-abdominal abscesses, peritonitis, or pleural space infections) who received multiple daily doses of caspofungin acetate for injection 50 mg, there was no significant effect of mild to end-stage renal impairment on caspofungin concentrations. No dosage adjustment is necessary for patients with renal impairment. Caspofungin is not dialyzable, thus supplementary dosing is not required following hemodialysis.

Hepatic Impairment

Plasma concentrations of caspofungin after a single 70 mg dose in adult patients with mild hepatic impairment (Child-Pugh score 5 to 6) were increased by approximately 55% in AUC compared to healthy control subjects. In a 14 day multiple-dose study (70 mg on Day 1 followed by 50 mg daily thereafter), plasma concentrations in adult patients with mild hepatic impairment were increased modestly (19 to 25% in AUC) on Days 7 and 14 relative to healthy control subjects. No dosage adjustment is recommended for patients with mild hepatic impairment.

Adult patients with moderate hepatic impairment (Child-Pugh score 7 to 9) who received a single 70 mg dose of caspofungin acetate for injection had an average plasma caspofungin increase of 76% in AUC compared to control subjects. A dosage reduction is recommended for adult patients with moderate hepatic impairment based upon these pharmacokinetic data [see Dosage and Administration (2.4)].

There is no clinical experience in adult patients with severe hepatic impairment (Child-Pugh score greater than

9) or in pediatric patients with any degree of hepatic impairment.

Gender

Plasma concentrations of caspofungin in healthy adult men and women were similar following a single 70 mg dose. After 13 daily 50 mg doses, caspofungin plasma concentrations in women were elevated slightly (approximately 22% in area under the curve [AUC]) relative to men. No dosage adjustment is necessary based on gender.

Race

Regression analyses of patient pharmacokinetic data indicated that no clinically significant differences in the pharmacokinetics of caspofungin were seen among Caucasians, Blacks, and Hispanics. No dosage adjustment is necessary on the basis of race.

Geriatric Patients

Plasma concentrations of caspofungin in healthy older men and women (65 years of age and older) were increased slightly (approximately 28% AUC) compared to young healthy men after a single 70 mg dose of caspofungin. In patients who were treated empirically or who had candidemia or other Candida infections (intra-abdominal abscesses, peritonitis, or pleural space infections), a similar modest effect of age was seen in older patients relative to younger patients. No dosage adjustment is necessary for the elderly [see Use in Specific Populations (8.5)].

Pediatric Patients

Caspofungin acetate for injection has been studied in five prospective studies involving pediatric patients under 18 years of age, including three pediatric pharmacokinetic studies [initial study in adolescents (12 to 17 years of age) and children (2 to 11 years of age) followed by a study in younger patients (3 to 23 months of age) and then followed by a study in neonates and infants (less than 3 months of age)] [see Use in Specific Populations (8.4)].

Pharmacokinetic parameters following multiple doses of caspofungin acetate for injection in pediatric and adult patients are presented in Table 8.

Table 8: Pharmacokinetic Parameters Following Multiple Doses of Caspofungin Acetate for Injection in Pediatric (3 months to 17 years) and Adult Patients
Population | N | Daily Dose | Pharmacokinetic Parameters (Mean ±Standard Deviation)
Population | N | Daily Dose | AUC0-24hr (mcg•hr/mL) | C1hr (mcg/mL) | C24hr (mcg/mL) | t1/2 (hr)* | CI (mL/min)
PEDIATRIC PATIENTS
Adolescents, Aged 12 to 17 years | 8 | 50 mg/m^2 | 124.9 ± 50.4 | 14.0 ± 6.9 | 2.4 ± 1.0 | 11.2 ± 1.7 | 12.6 ± 5.5
Children, Aged 2 to 11 years | 9 | 50 mg/m^2 | 120.0 ± 33.4 | 16.1 ± 4.2 | 1.7 ± 0.8 | 8.2 ± 2.4 | 6.4 ± 2.6
Young Children, Aged 3 to 23 months | 8 | 50 mg/m^2 | 131.2 ± 17.7 | 17.6 ± 3.9 | 1.7 ± 0.7 | 8.8 ± 2.1 | 3.2 ± 0.4
ADULT PATIENTS
Adults with Esophageal Candidiasis | 6† | 50 mg | 87.3 ± 30.0 | 8.7 ± 2.1 | 1.7 ± 0.7 | 13.0 ± 1.9 | 10.6 ± 3.8
Adults receiving Empirical Therapy | 119‡ | 50 mg§ | -- | 8.0 ± 3.4 | 1.6 ± 0.7 | -- | --
* Harmonic Mean ± jackknife standard deviation.
† N=5 for C1hr and AUC0-24hr; N=6 for C24hr .
‡ N=117 for C24hr; N=119 for C1hr .
§ Following an initial 70 mg loading dose on day 1.

Drug Interactions [see Drug Interactions (7)]

Studies in vitro show that caspofungin acetate is not an inhibitor of any enzyme in the cytochrome P (CYP) system. Caspofungin is not a substrate for P-glycoprotein and is a poor substrate for CYP enzymes.

In clinical studies, caspofungin did not induce the CYP3A4 metabolism of other drugs. Clinical studies in adult healthy volunteers also demonstrated that the pharmacokinetics of caspofungin are not altered by itraconazole, amphotericin B, mycophenolate, nelfinavir, or tacrolimus. Caspofungin has no effect on the pharmacokinetics of itraconazole, amphotericin B, or the active metabolite of mycophenolate.

Cyclosporine: In two adult clinical studies, cyclosporine (one 4 mg/kg dose or two 3 mg/kg doses) increased the AUC of caspofungin by approximately 35%. Caspofungin acetate for injection did not increase the plasma levels of cyclosporine. There were transient increases in liver ALT and AST when caspofungin acetate for injection and cyclosporine were co-administered [see Warnings and Precautions (5.2)].

Tacrolimus: Caspofungin acetate for injection reduced the blood AUC0-12 of tacrolimus (FK-506, Prograf ®) by approximately 20%, peak blood concentration (Cmax) by 16%, and 12 hour blood concentration (C12hr) by 26% in healthy adult subjects when tacrolimus (2 doses of 0.1 mg/kg 12 hours apart) was administered on the 10th day of caspofungin acetate for injection 70 mg daily, as compared to results from a control period in which tacrolimus was administered alone. For patients receiving both therapies, standard monitoring of tacrolimus whole blood trough concentrations and appropriate tacrolimus dosage adjustments are recommended.

Rifampin: A drug-drug interaction study with rifampin in adult healthy volunteers has shown a 30% decrease in caspofungin trough concentrations [see Dosage and Administration (2.5)].

Other Inducers of Hepatic CYP Enzymes

Adults: Results from regression analyses of adult patient pharmacokinetic data suggest that co-administration of other hepatic CYP enzyme inducers (e.g., efavirenz, nevirapine, phenytoin, dexamethasone, or carbamazepine) with caspofungin acetate for injection may result in clinically meaningful reductions in caspofungin concentrations. It is not known which drug clearance mechanism involved in caspofungin disposition may be inducible [see Dosage and Administration (2.5)].

Pediatric patients: In pediatric patients, results from regression analyses of pharmacokinetic data suggest that co-administration of dexamethasone with caspofungin acetate for injection may result in clinically meaningful reductions in caspofungin trough concentrations. This finding may indicate that pediatric patients will have similar reductions with inducers as seen in adults [see Dosage and Administration (2.5)].

12.4 Microbiology

Mechanism of Action

Caspofungin, an echinocandin, inhibits the synthesis of beta (1,3)-D-glucan, an essential component of the cell wall of susceptible Aspergillus species and Candida species. Beta (1,3)-D-glucan is not present in mammalian cells. Caspofungin has shown activity against Candida species and in regions of active cell growth of the hyphae of Aspergillus fumigatus.

Resistance

There have been reports of clinical failures in patients receiving caspofungin therapy due to the development of drug resistant Candida or Aspergillus species. Some of these reports have identified specific mutations in the Fks subunits, encoded by the fks1 and/or fks2 genes, of the glucan synthase enzyme. These mutations are associated with higher MICs and breakthrough infection. Candida species that exhibit reduced susceptibility to caspofungin as a result of an increase in the chitin content of the fungal cell wall have also been identified, although the significance of this phenomenon in vivo is not well known.

Interactions With Other Antimicrobials

Studies in vitro and in vivo of caspofungin, in combination with amphotericin B, suggest no antagonism of antifungal activity against either A. fumigatus or C. albicans. The clinical significance of these results is unknown.

Antimicrobial Activity

Caspofungin has been shown to be active against most strains of the following microorganisms both in vitro and in clinical infections [see Indications and Usage (1)]:

Aspergillus flavus
Aspergillus fumigatus
Aspergillus terreus
Candida albicans
Candida glabrata
Candida guilliermondii
Candida krusei
Candida parapsilosis
Candida tropicalis

Susceptibility Testing

For specific information regarding susceptibility test interpretive criteria and associated test methods and quality control standards recognized by FDA for this drug, please see: https://www.fda.gov/STIC.

13 NONCLINICAL TOXICOLOGY

13.1 Carcinogenesis, Mutagenesis, Impairment of Fertility

No long-term studies in animals have been performed to evaluate the carcinogenic potential of caspofungin.

Caspofungin did not show evidence of mutagenic or genotoxic potential when evaluated in the following in vitro assays: bacterial (Ames) and mammalian cell (V79 Chinese hamster lung fibroblasts) mutagenesis assays, the alkaline elution/rat hepatocyte DNA strand break test, and the chromosome aberration assay in Chinese hamster ovary cells. Caspofungin was not genotoxic when assessed in the mouse bone marrow chromosomal test at doses up to 12.5 mg/kg (equivalent to a human dose of 1 mg/kg based on body surface area comparisons), administered intravenously.

Fertility and reproductive performance were not affected by the intravenous administration of caspofungin to rats at doses up to 5 mg/kg. At 5 mg/kg exposures were similar to those seen in patients treated with the 70 mg dose.

13.2 Animal Toxicology and/or Pharmacology

In one 5 week study in monkeys at doses which produced exposures approximately 4 to 6 times those seen in adult patients treated with a 70 mg dose, scattered small foci of subcapsular necrosis were observed microscopically in the livers of some animals (2/8 monkeys at 5 mg/kg and 4/8 monkeys at 8 mg/kg); however, this histopathological finding was not seen in another study of 27 weeks duration at similar doses.

No treatment-related findings were seen in a 5-week study in infant monkeys at doses which produced exposures approximately 3 times those achieved in pediatric patients receiving a maintenance dose of 50 mg/m^2 daily.

14 CLINICAL STUDIES

14.1 Empirical Therapy in Febrile, Neutropenic Patients

A double-blind study enrolled 1,111 febrile, neutropenic (less than 500 cells/mm^3) patients who were randomized to treatment with daily doses of caspofungin acetate for injection (50 mg/day following a 70 mg loading dose on Day 1) or AmBisome (3 mg/kg/day). Patients were stratified based on risk category (high-risk patients had undergone allogeneic stem cell transplantation or had relapsed acute leukemia) and on receipt of prior antifungal prophylaxis. Twenty-four percent of patients were high risk and 56% had received prior antifungal prophylaxis. Patients who remained febrile or clinically deteriorated following 5 days of therapy could receive 70 mg/day of caspofungin acetate for injection or 5 mg/kg/day of AmBisome. Treatment was continued to resolution of neutropenia (but not beyond 28 days unless a fungal infection was documented).

An overall favorable response required meeting each of the following criteria: no documented breakthrough fungal infections up to 7 days after completion of treatment, survival for 7 days after completion of study therapy, no discontinuation of the study drug because of drug-related toxicity or lack of efficacy, resolution of fever during the period of neutropenia, and successful treatment of any documented baseline fungal infection.

Based on the composite response rates, caspofungin acetate for injection was as effective as AmBisome in empirical therapy of persistent febrile neutropenia (see Table 9).

Table 9: Favorable Response of Patients with Persistent Fever and Neutropenia
 | Caspofungin Acetate for Injection* | AmBisome* | % Difference (Confidence Interval)
Number of Patients‡ | 556 | 539
Overall Favorable Response | 190 (33.9%) | 181 (33.7%) | 0.2 (-5.6, 6.0)
No documented breakthrough fungal infection | 527 (94.8%) | 515 (95.5%) | -0.8
Survival 7 days after end of treatment | 515 (92.6%) | 481 (89.2%) | 3.4
No discontinuation due to toxicity or lack of efficacy | 499 (89.7%) | 461 (85.5%) | 4.2
Resolution of fever during neutropenia | 229 (41.2%) | 223 (41.4%) | -0.2
* Caspofungin acetate for injection: 70 mg on Day 1, then 50 mg once daily for the remainder of treatment (daily dose increased to 70 mg for 73 patients); AmBisome: 3 mg/kg/day (daily dose increased to 5 mg/kg for 74 patients).
† Overall Response: estimated % difference adjusted for strata and expressed as caspofungin acetate for injection
– AmBisome (95.2% CI); Individual criteria presented above are not mutually exclusive. The percent difference calculated as caspofungin acetate for injection – AmBisome.
‡ Analysis population excluded subjects who did not have fever or neutropenia at study entry.

The rate of successful treatment of documented baseline infections, a component of the primary endpoint, was not statistically different between treatment groups.

The response rates did not differ between treatment groups based on either of the stratification variables: risk category or prior antifungal prophylaxis.

14.2 Candidemia and the Following Other Candida Infections: Intra-Abdominal Abscesses, Peritonitis and Pleural Space Infections

In a randomized, double-blind study, patients with a proven diagnosis of invasive candidiasis received daily doses of caspofungin acetate for injection (50 mg/day following a 70 mg loading dose on Day 1) or amphotericin B deoxycholate (0.6 to 0.7 mg/kg/day for non-neutropenic patients and 0.7 to 1 mg/kg/day for neutropenic patients). Patients were stratified by both neutropenic status and APACHE II score. Patients with Candida endocarditis, meningitis, or osteomyelitis were excluded from this study.

Patients who met the entry criteria and received one or more doses of intravenous (IV) study therapy were included in the modified intention-to-treat [MITT] analysis of response at the end of intravenous (IV) study therapy. A favorable response at this time point required both symptom/sign resolution/improvement and microbiological clearance of the Candida infection.

Two hundred thirty-nine patients were enrolled. Patient disposition is shown in Table 10.

Table 10: Disposition in Candidemia and Other Candida Infections (Intra-abdominal abscesses, peritonitis, and pleural space infections)
 | Caspofungin Acetate for Injection * | Amphotericin B
Randomized patients | 114 | 125
Patients completing study† | 63 (55.3%) | 69 (55.2%)
DISCONTINUATIONS OF STUDY†
All Study Discontinuations | 51 (44.7%) | 56 (44.8%)
Study Discontinuations due to clinical adverse events | 39 (34.2%) | 43 (34.4%)
Study Discontinuations due to laboratory adverse events | 0 (0%) | 1 (0.8%)
DISCONTINUATIONS OF STUDY THERAPY
All Study Therapy Discontinuations | 48 (42.1%) | 58 (46.4%)
Study Therapy Discontinuations due to clinical adverse events | 30 (26.3%) | 37 (29.6%)
Study Therapy Discontinuations due to laboratory adverse events | 1 (0.9%) | 7 (5.6%)
Study Therapy Discontinuations due to all drug- related‡ adverse events | 3 (2.6%) | 29 (23.2%)
* Patients received caspofungin acetate for injection 70 mg on Day 1, then 50 mg once daily for the remainder of their treatment.
† Study defined as study treatment period and 6 to 8-week follow-up period.
‡ Determined by the investigator to be possibly, probably, or definitely drug-related.

Of the 239 patients enrolled, 224 met the criteria for inclusion in the MITT population (109 treated with caspofungin acetate for injection and 115 treated with amphotericin B). Of these 224 patients, 186 patients had candidemia (92 treated with caspofungin acetate for injection and 94 treated with amphotericin B). The majority of the patients with candidemia were non-neutropenic (87%) and had an APACHE II score less than or equal to 20 (77%) in both arms. Most candidemia infections were caused by C. albicans (39%), followed by C. parapsilosis (20%), C. tropicalis (17%), C. glabrata (8%), and C. krusei (3%).

At the end of intravenous (IV) study therapy, caspofungin acetate for injection was comparable to amphotericin B in the treatment of candidemia in the MITT population. For the other efficacy time points (Day 10 of intravenous (IV) study therapy, end of all antifungal therapy, 2-week post-therapy follow-up, and 6- to 8-week post-therapy follow-up), caspofungin acetate for injection was as effective as amphotericin B.

Outcome, relapse and mortality data are shown in Table 11.

Table 11: Outcomes, Relapse, & Mortality in Candidemia and Other Candida Infections (Intra- abdominal abscesses, peritonitis, and pleural space infections)
 | Caspofungin Acetate for Injection * | Amphotericin B | % Difference† after adjusting for strata (Confidence Interval)‡
Number of MITT§ patients | 109 | 115
FAVORABLE OUTCOMES (MITT) AT THE END OF INTRAVENOUS
(IV) STUDY THERAPY
All MITT patients | 81/109 (74.3%) | 78/115 (67.8%) | 7.5 (-5.4, 20.3)
Candidemia | 67/92 (72.8%) | 63/94 (67.0%) | 7.0 (-7.0, 21.1)
Neutropenic | 6/14 (43%) | 5/10 (50%)
Non-neutropenic | 61/78 (78%) | 58/84 (69%)
Endophthalmitis | 0/1 | 2/3
Multiple Sites | 4/5 | 4/4
Blood / Pleural | 1/1 | 1/1
Blood / Peritoneal | 1/1 | 1/1
Blood / Urine | - | 1/1
Peritoneal / Pleural | 1/2 | -
Abdominal / Peritoneal | - | 1/1
Subphrenic / Peritoneal | 1/1 | -
DISSEMINATED INFECTIONS, RELAPSES AND MORTALITY
Disseminated Infections in neutropenic patients | 4/14 (28.6%) | 3/10 (30.0%)
All relapses¶ | 7/81 (8.6%) | 8/78 (10.3%)
Culture-confirmed relapse | 5/81 (6%) | 2/78 (3%)
Overall study# mortality in MITT | 36/109 (33.0%) | 35/115 (30.4%)
Mortality during study therapy | 18/109 (17%) | 13/115 (11%)
Mortality attributed to Candida | 4/109 (4%) | 7/115 (6%)
*Patients received caspofungin acetate for injection 70 mg on Day 1, then 50 mg once daily for the remainder of their treatment.
† Calculated as caspofungin acetate for injection - amphotericin B.
‡ 95% CI for candidemia, 95.6% for all patients.
§ Modified intention-to-treat.
¶ Includes all patients who either developed a culture-confirmed recurrence of Candida infection or required antifungal therapy for the treatment of a proven or suspected Candida infection in the follow-up period.
# Study defined as study treatment period and 6 to 8 week follow-up period.
In this study, the efficacy of caspofungin acetate for injection in patients with intra-abdominal abscesses, peritonitis and pleural space Candida infections was evaluated in 19 non-neutropenic patients. Two of these patients had concurrent candidemia. Candida was part of a polymicrobial infection that required adjunctive surgical drainage in 11 of these 19 patients. A favorable response was seen in 9 of 9 patients with peritonitis, 3 of 4 with abscesses (liver, parasplenic, and urinary bladder abscesses), 2 of 2 with pleural space infections, 1 of 2 with mixed peritoneal and pleural infection, 1 of 1 with mixed abdominal abscess and peritonitis, and 0 of 1 with Candida pneumonia.

Overall, across all sites of infection included in the study, the efficacy of caspofungin acetate for injection was comparable to that of amphotericin B for the primary endpoint.

In this study, the efficacy data for caspofungin acetate for injection in neutropenic patients with candidemia were limited. In a separate compassionate use study, 4 patients with hepatosplenic candidiasis received prolonged therapy with caspofungin acetate for injection following other long-term antifungal therapy; three of these patients had a favorable response.

In a second randomized, double-blind study, 197 patients with proven invasive candidiasis received caspofungin acetate for injection 50 mg/day (following a 70 mg loading dose on Day 1) or caspofungin acetate for injection 150 mg/day. The diagnostic criteria, evaluation time points, and efficacy endpoints were similar to those employed in the prior study. Patients with Candida endocarditis, meningitis, or osteomyelitis were excluded.

Although this study was designed to compare the safety of the two doses, it was not large enough to detect differences in rare or unexpected adverse events [see Adverse Reactions (6.1)]. The efficacy of caspofungin acetate for injection at the 150 mg daily dose was not significantly better than the efficacy of the 50 mg daily dose of caspofungin acetate for injection. The efficacy of doses higher than 50 mg daily in the other adult patients for whom caspofungin acetate for injection is indicated has not been evaluated.

14.3 Esophageal Candidiasis (and information on oropharyngeal candidiasis)

The safety and efficacy of caspofungin acetate for injection in the treatment of esophageal candidiasis was evaluated in one large, controlled, noninferiority, clinical trial and two smaller dose-response studies.

In all 3 studies, patients were required to have symptoms and microbiological documentation of esophageal candidiasis; most patients had advanced AIDS (with CD4 counts less than 50/mm^3).

Of the 166 patients in the large study who had culture-confirmed esophageal candidiasis at baseline, 120 had Candida albicans and 2 had Candida tropicalis as the sole baseline pathogen whereas 44 had mixed baseline cultures containing C. albicans and one or more additional Candida species.

In the large, randomized, double-blind study comparing caspofungin acetate for injection 50 mg/day versus intravenous fluconazole 200 mg/day for the treatment of esophageal candidiasis, patients were treated for an average of 9 days (range 7 to 21 days). Favorable overall response at 5- to 7-days following discontinuation of study therapy required both complete resolution of symptoms and significant endoscopic improvement. The definition of endoscopic response was based on severity of disease at baseline using a 4-grade scale and required at least a two-grade reduction from baseline endoscopic score or reduction to grade 0 for patients with a baseline score of 2 or less.

The proportion of patients with a favorable overall response was comparable for caspofungin acetate for injection and fluconazole as shown in Table 12.

Table 12: Favorable Response Rates for Patients with Esophageal Candidiasis*
 | Caspofungin Acetate for Injection | Fluconazole | % Difference † (95% CI)
Day 5 to 7 post-treatment | 66/81 (81.5%) | 80/94 (85.1%) | -3.6 (-14.7, 7.5)
* Analysis excluded patients without documented esophageal candidiasis or patients not receiving at least 1 day of study therapy.
† Calculated as caspofungin acetate for injection – fluconazole.

The proportion of patients with a favorable symptom response was also comparable (90.1% and 89.4% for caspofungin acetate for injection and fluconazole, respectively). In addition, the proportion of patients with a favorable endoscopic response was comparable (85.2% and 86.2% for caspofungin acetate for injection and fluconazole, respectively).

As shown in Table 13, the esophageal candidiasis relapse rates at the Day 14 post-treatment visit were similar for the two groups. At the Day 28 post-treatment visit, the group treated with caspofungin acetate for injection had a numerically higher incidence of relapse; however, the difference was not statistically significant.

Table 13: Relapse Rates at 14 and 28 Days Post-Therapy in Patients with Esophageal Candidiasis at Baseline
 | Caspofungin Acetate for Injection | Fluconazole | % Difference* (95% CI)
Day 14 post-treatment | 7/66 (10.6%) | 6/76 (7.9%) | 2.7 (-6.9, 12.3)
Day 28 post-treatment | 18/64 (28.1%) | 12/72 (16.7%) | 11.5 (-2.5, 25.4)
* Calculated as caspofungin acetate for injection – fluconazole.

In this trial, which was designed to establish noninferiority of caspofungin acetate for injection to fluconazole for the treatment of esophageal candidiasis, 122 (70%) patients also had oropharyngeal candidiasis. A favorable response was defined as complete resolution of all symptoms of oropharyngeal disease and all visible oropharyngeal lesions. The proportion of patients with a favorable oropharyngeal response at the 5- to 7-day post-treatment visit was numerically lower for caspofungin acetate for injection; however, the difference was not statistically significant. Oropharyngeal candidiasis relapse rates at Day 14 and Day 28 post-treatment visits were statistically significantly higher for caspofungin acetate for injection than for fluconazole. The results are shown in Table 14.

Table 14: Oropharyngeal Candidiasis Response Rates at 5 to 7 Days Post-Therapy and Relapse Rates at 14 and 28 Days Post-Therapy in Patients with Oropharyngeal and Esophageal Candidiasis at Baseline
 | Caspofungin Acetate for Injection | Fluconazole | % Difference* (95% CI)
Response Rate Day 5 to 7 post-treatment | 40/56 (71.4%) | 55/66 (83.3%) | -11.9 (-26.8, 3.0)
Relapse Rate Day 14 post-treatment | 17/40 (42.5%) | 7/53 (13.2%) | 29.3 (11.5, 47.1)
Relapse Rate Day 28 post-treatment | 23/39 (59.0%) | 18/51 (35.3%) | 23.7 (3.4, 43.9)
* Calculated as caspofungin acetate for injection – fluconazole.

The results from the two smaller dose-ranging studies corroborate the efficacy of caspofungin acetate for injection for esophageal candidiasis that was demonstrated in the larger study.

Caspofungin acetate for injection was associated with favorable outcomes in 7 of 10 esophageal C. albicans infections refractory to at least 200 mg of fluconazole given for 7 days, although the in vitro susceptibility of the infecting isolates to fluconazole was not known.

14.4 Invasive Aspergillosis

Sixty-nine patients between the ages of 18 and 80 with invasive aspergillosis were enrolled in an open-label, noncomparative study to evaluate the safety, tolerability, and efficacy of caspofungin acetate for injection.

Enrolled patients had previously been refractory to or intolerant of other antifungal therapy(ies). Refractory patients were classified as those who had disease progression or failed to improve despite therapy for at least 7 days with amphotericin B, lipid formulations of amphotericin B, itraconazole, or an investigational azole with reported activity against Aspergillus. Intolerance to previous therapy was defined as a doubling of creatinine (or creatinine 2.5 mg/dL or greater while on therapy), other acute reactions, or infusion-related toxicity. To be included in the study, patients with pulmonary disease must have had definite (positive tissue histopathology or positive culture from tissue obtained by an invasive procedure) or probable (positive radiographic or computed tomography evidence with supporting culture from bronchoalveolar lavage or sputum, galactomannan enzyme- linked immunosorbent assay, and/or polymerase chain reaction) invasive aspergillosis. Patients with extrapulmonary disease had to have definite invasive aspergillosis. Patients were administered a single 70 mg loading dose of caspofungin acetate for injection and subsequently dosed with 50 mg daily. The mean duration of therapy was 33.7 days, with a range of 1 to 162 days. An independent expert panel evaluated patient data, including diagnosis of invasive aspergillosis, response and tolerability to previous antifungal therapy, treatment course on caspofungin acetate for injection, and clinical outcome.

A favorable response was defined as either complete resolution (complete response) or clinically meaningful improvement (partial response) of all signs and symptoms and attributable radiographic findings. Stable, nonprogressive disease was considered to be an unfavorable response.

Among the 69 patients enrolled in the study, 63 met entry diagnostic criteria and had outcome data; and of these, 52 patients received treatment for greater than 7 days. Fifty-three (84%) were refractory to previous antifungal therapy and 10 (16%) were intolerant. Forty-five patients had pulmonary disease and 18 had extrapulmonary disease. Underlying conditions were hematologic malignancy (N=24), allogeneic bone marrow transplant or stem cell transplant (N=18), organ transplant (N=8), solid tumor (N=3), or other conditions (N=10). All patients in the study received concomitant therapies for their other underlying conditions. Eighteen patients received tacrolimus and caspofungin acetate for injection concomitantly, of whom 8 also received mycophenolate mofetil.

Overall, the expert panel determined that 41% (26/63) of patients receiving at least one dose of caspofungin acetate for injection had a favorable response. For those patients who received greater than 7 days of therapy with caspofungin acetate for injection, 50% (26/52) had a favorable response. The favorable response rates for patients who were either refractory to or intolerant of previous therapies were 36% (19/53) and 70% (7/10), respectively. The response rates among patients with pulmonary disease and extrapulmonary disease were 47% (21/45) and 28% (5/18), respectively. Among patients with extrapulmonary disease, 2 of 8 patients who also had definite, probable, or possible CNS involvement had a favorable response. Two of these 8 patients had progression of disease and manifested CNS involvement while on therapy.

Caspofungin acetate for injection is effective for the treatment of invasive aspergillosis in patients who are refractory to or intolerant of itraconazole, amphotericin B, and/or lipid formulations of amphotericin B. However, the efficacy of caspofungin acetate for injection for initial treatment of invasive aspergillosis has not been evaluated in comparator-controlled clinical studies.

14.5 Pediatric Patients

The safety and efficacy of caspofungin acetate for injection were evaluated in pediatric patients 3 months to 17 years of age in two prospective, multicenter clinical trials.

The first study, which enrolled 82 patients between 2 to 17 years of age, was a randomized, double-blind study comparing caspofungin acetate for injection (50 mg/m^2 intravenously once daily following a 70 mg/m^2 loading dose on Day 1 [not to exceed 70 mg daily]) to AmBisome (3 mg/kg intravenously daily) in a 2:1 treatment fashion (56 on caspofungin, 26 on AmBisome) as empirical therapy in pediatric patients with persistent fever and neutropenia. The study design and criteria for efficacy assessment were similar to the study in adult patients [see Clinical Studies (14.1)]. Patients were stratified based on risk category (high-risk patients had undergone allogeneic stem cell transplantation or had relapsed acute leukemia). Twenty-seven percent of patients in both treatment groups were high risk. Favorable overall response rates of pediatric patients with persistent fever and neutropenia are presented in Table 17.

Table 17: Favorable Overall Response Rates of Pediatric Patients with Persistent Fever and Neutropenia
 | Caspofungin Acetate for Injection | AmBisome*
Number of Patients | 56 | 25
Overall Favorable Response | 26/56 (46.4%) | 8/25 (32.0%)
High risk | 9/15 (60.0%) | 0/7 (0.0%)
Low risk | 17/41 (41.5%) | 8/18 (44.4%)
* One patient excluded from analysis due to no fever at study entry.

The second study was a prospective, open-label, non-comparative study estimating the safety and efficacy of caspofungin in pediatric patients (ages 3 months to 17 years) with candidemia and other Candida infections, esophageal candidiasis, and invasive aspergillosis (as salvage therapy). The study employed diagnostic criteria which were based on established EORTC/MSG criteria of proven or probable infection; these criteria were similar to those criteria employed in the adult studies for these various indications. Similarly, the efficacy time points and endpoints used in this study were similar to those employed in the corresponding adult studies [see Clinical Studies (14.2,14.3, and 14.4)]. All patients received caspofungin acetate for injection at 50 mg/m^2 intravenously once daily following a 70 mg/m^2 loading dose on Day 1 (not to exceed 70 mg daily). Among the 49 enrolled patients who received caspofungin acetate for injection, 48 were included in the efficacy analysis (one patient excluded due to not having a baseline Aspergillus or Candida infection). Of these 48 patients, 37 had candidemia or other Candida infections, 10 had invasive aspergillosis, and 1 patient had esophageal candidiasis. Most candidemia and other Candida infections were caused by C. albicans (35%), followed by C. parapsilosis (22%), C. tropicalis (14%), and C. glabrata (11%). The favorable response rate, by indication, at the end of caspofungin therapy was as follows: 30/37 (81%) in candidemia or other Candida infections, 5/10 (50%) in invasive aspergillosis, and 1/1 in esophageal candidiasis.

15 REFERENCES

1. Mosteller RD: Simplified Calculation of Body Surface Area. N Engl J Med 1987 Oct 22;317(17): 1098 (letter).

16 HOW SUPPLIED/STORAGE AND HANDLING

How Supplied

Caspofungin acetate for Injection is a lyophilized white to off-white cake or powder for intravenous infusion, supplied in single-dose vials with a rubber stopper and an aluminum seal as follows:

Product Code | Caspofungin Acetate for Injection Total Product Strength (Concentration) | Carton NDC and Package Configuration | Vial NDC
356110 | 50 mg per vial | 63323-356-10 10 Single-Dose Vials | 63323-356-01
358110 | 70 mg per vial | 63323-358-10 10 Single-Dose Vials | 63323-358-01

Storage and Handling

The lyophilized vials should be stored at 20° to 25°C (68° to 77°F) [see USP Controlled Room Temperature].

Reconstituted Concentrate

Reconstituted Caspofungin acetate for Injection in the vial may be stored at ≤ 25°C (≤ 77°F) for one hour prior to the preparation of the patient infusion solution.

Diluted Product

The final patient infusion solution in the intravenous bag or bottle can be stored at ≤ 25°C (≤ 77°F) for 24 hours or at 2° to 8°C (36° to 46°F) for 48 hours.

The container closure is not made with natural rubber latex.

17 PATIENT COUNSELING INFORMATION

Hypersensitivity

Inform patients that anaphylactic reactions have been reported during administration of caspofungin acetate for injection. Caspofungin acetate for Injection can cause hypersensitivity reactions, including rash, facial swelling, angioedema, pruritus, sensation of warmth, or bronchospasm. Inform patients to report these signs or symptoms to their healthcare providers.

Hepatic Effects

Inform patients that there have been isolated reports of serious hepatic effects from caspofungin acetate for injection therapy.

Use in Pregnancy and Breastfeeding Mothers

Advise female patients of the potential risks to a fetus. Instruct patients to tell their healthcare provider if they are pregnant, become pregnant, or are thinking about becoming pregnant. Instruct patients to tell their healthcare provider if they plan to breastfeed their infant.

The brand names mentioned in this document are the trademarks of their respective owners.

Lake Zurich, IL 60047

www.fresenius-kabi.com/us

451328D

PACKAGE LABEL

PACKAGE LABEL - PRINCIPAL DISPLAY - Caspofungin Acetate- 50 mg Single-Dose Vial Label
Caspofungin Acetate for Injection
50 mg per vial*
For intravenous infusion after dilution.
Preservative free.
Discard unused portion.
Single-Dose Vial
Rx only

PACKAGE LABEL

PACKAGE LABEL - PRINCIPAL DISPLAY - Caspofungin Acetate- 50 mg Single-Dose Vial Carton Panel
NDC 63323-356-10
Caspofungin Acetate for Injection
50 mg per vial*
For intravenous infusion after dilution.
Preservative free.
Discard unused portion.
Rx only
10 Single-Dose Vials

Do not use Diluents
containing Dextrose
(α-D-glucose)

PACKAGE LABEL

PACKAGE LABEL - PRINCIPAL DISPLAY - Caspofungin Acetate - 70 mg Single-Dose Vial Label
Caspofungin Acetate for Injection
70 mg per vial*
For intravenous infusion after dilution.
Preservative free.
Discard unused portion.
Single-Dose Vial
Rx only

PACKAGE LABEL

PACKAGE LABEL - PRINCIPAL DISPLAY - Caspofungin Acetate - 70 mg Single-Dose Vial Carton Panel
NDC 63323-358-10
Caspofungin Acetate for Injection
70 mg per vial*
For intravenous infusion after dilution.
Preservative free.
Discard unused portion.
Rx only
10 Single-Dose Vials

Do not use Diluents
containing Dextrose
(α-D-glucose)